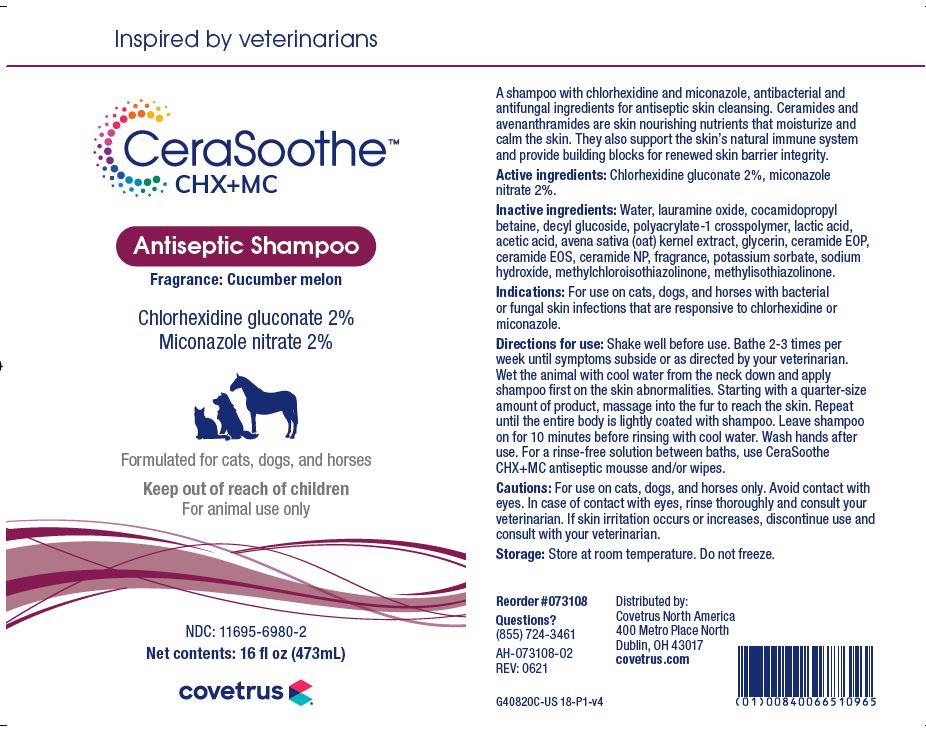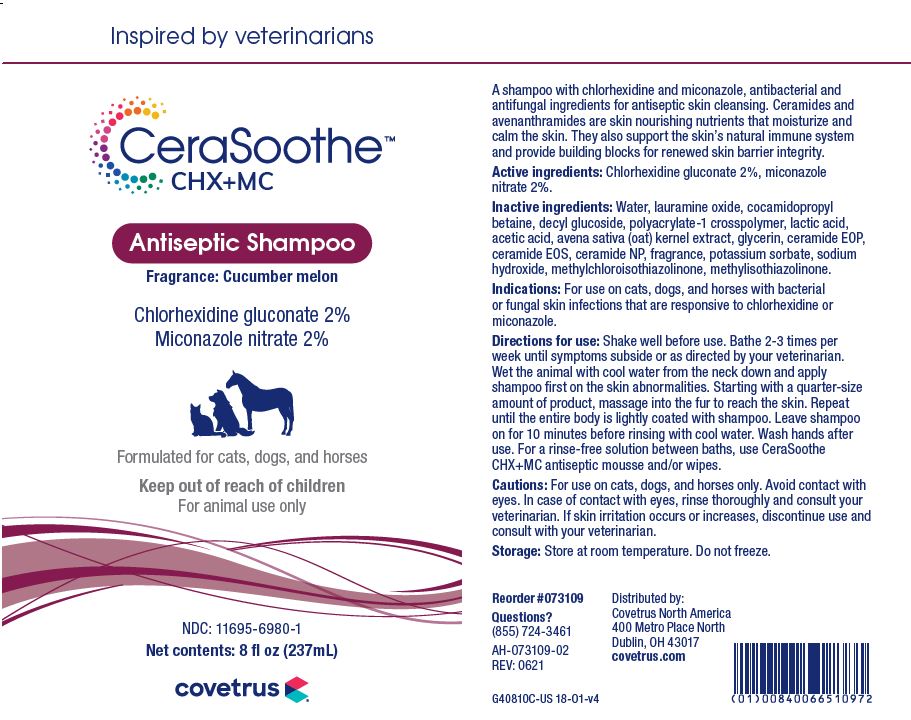 DRUG LABEL: CeraSoothe
NDC: 11695-6980 | Form: SHAMPOO
Manufacturer: BUTLER ANIMAL HEALTH SUPPLY, LLC DBA COVETRUS NORTH AMERICA
Category: animal | Type: OTC ANIMAL DRUG LABEL
Date: 20220609

ACTIVE INGREDIENTS: CHLORHEXIDINE GLUCONATE 20 mg/1 mL; MICONAZOLE NITRATE 20 mg/1 mL
INACTIVE INGREDIENTS: WATER; LAURAMINE OXIDE; COCAMIDOPROPYL BETAINE; DECYL GLUCOSIDE; CARBOMER HOMOPOLYMER, UNSPECIFIED TYPE; LACTIC ACID; ACETIC ACID; AVENANTHRAMIDES; GLYCERIN; CERAMIDE 1; CERAMIDE EOS; CERAMIDE NP; POTASSIUM SORBATE; SODIUM HYDROXIDE; METHYLCHLOROISOTHIAZOLINONE; METHYLISOTHIAZOLINONE

DESCRIPTION

CeraSoothe CHX+MC

Antiseptic Shampoo

Fragrance: Cucumber melon

Formulated for cats, dogs, and horses

A shampoo with chlorhexidine and miconazole, antibacterial and antifungal ingredients for skin cleansing. Ceramides and avenanthramides are skin nourishing nutrients that moisturize and calm the skin. They also support the skin’s natural immune system and provide building blocks for renewed skin barrier integrity.

Active ingredients: Chlorhexidine gluconate 2%, miconazole nitrate 2%.

Inactive ingredients: Water, lauramine oxide, cocamidopropyl betaine, decyl glucoside, polyacrylate-1 crosspolymer, lactic acid, acetic acid, avena sativa (oat) kernel extract, glycerin, ceramide EOP, ceramide EOS, ceramide NP, fragrance, potassium sorbate, sodium hydroxide, methylchloroisothiazolinone, methylisothiazoline.

INDICATIONS AND USAGE

Indications: For use on cats, dogs and horses with bacterial or fungal skin infections that are responsive to chlorhexidine or miconazole.

Directions for use: Shake well before use. Bathe 2-3 times per week until symptoms subside or as directed by your veterinarian. Wet the animal with cool water from the neck down and apply shampoo first on the skin abnormalities. Starting with a quarter-size amount of product, massage into the fur to reach the skin. Repeat until the entire body is lightly coated with shampoo. Leave shampoo on for 10 minutes before rinsing with cool water. Wash hands after use. For a rinse-free solution between baths, use CeraSoothe CHX+MC antiseptic mousse and/or wipes.

WARNINGS AND PRECAUTIONS

Cautions: For external use on cats, dogs, and horses only. Avoid contact with eyes. In case of contact with eyes, rinse thoroughly and consult your veterinarian. If skin irritation occurs or increases, discontinue use and consult with your veterinarian.

Storage: Store at room temperature. Do not freeze.

QUESTIONS?

(855) 724-3461

Distributed by:

Covetrus North America

400 Metro Place North

Dublin, OH 43017

covetrus.com

PRINCIPAL DISPLAY PANEL - 8 OUNCE (237 mL) Bottle

Inspired by veterinarians

CeraSoothe CHX+MC

Antiseptic Shampoo

Fragrance: Cucumber melon

Chlorhexidine gluconate 2%

Miconazole nitrate 2%

Formulated for cats, dogs, and horses

Keep out of reach of children

For animal use only

NDC: 11695-6980-1

Net contents: 8 fl oz (237 mL)

PRINCIPAL DISPLAY PANEL - 16 OUNCE (473 mL) Bottle

Inspired by veterinarians

CeraSoothe CHX+MC

Antiseptic Shampoo

Fragrance: Cucumber melon

Chlorhexidine gluconate 2%

Miconazole nitrate 2%

Formulated for cats, dogs, and horses

Keep out of reach of children

For animal use only

NDC: 11695-6980-2

Net contents: 16 fl oz (473 mL)